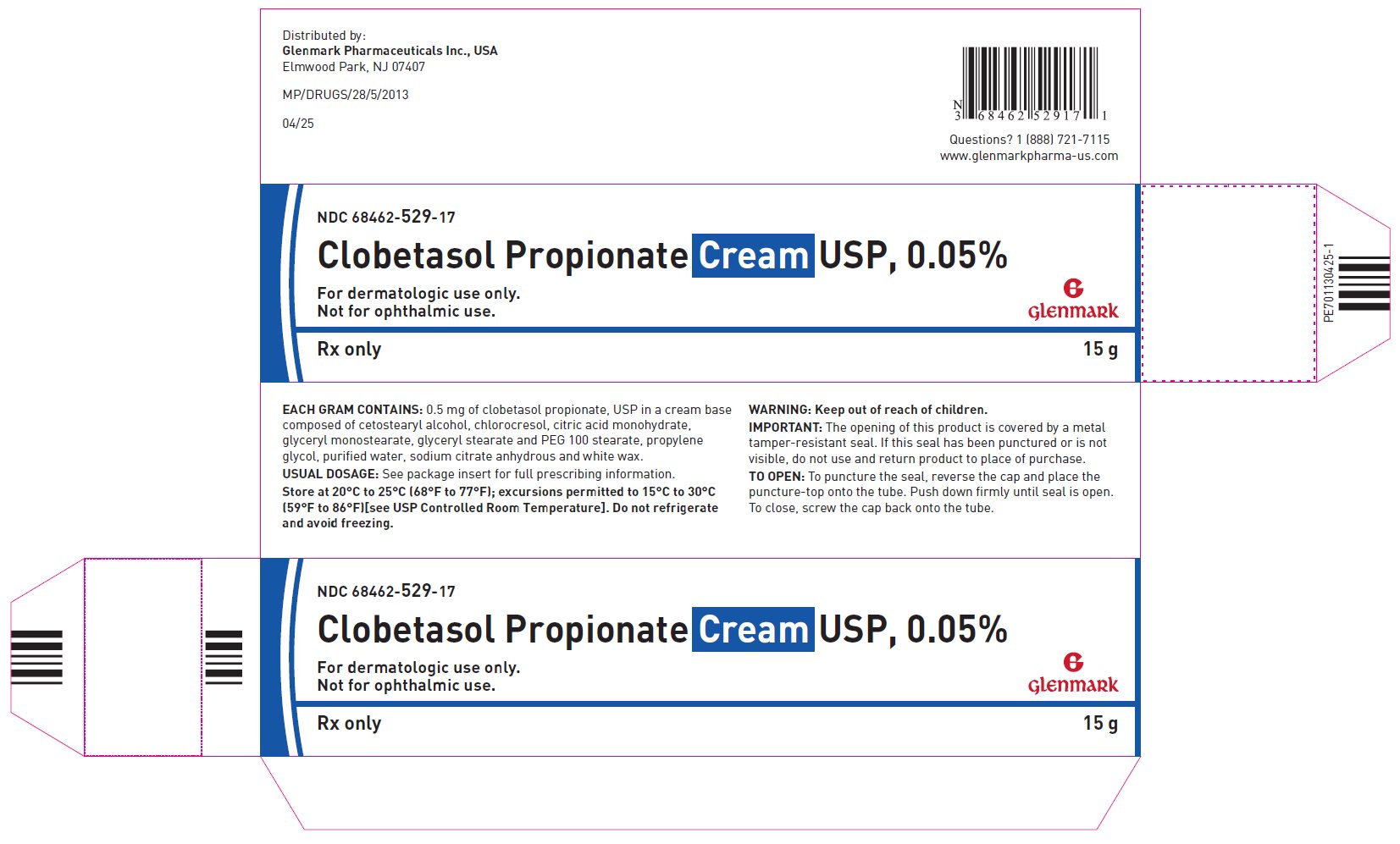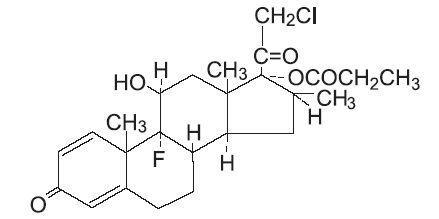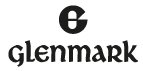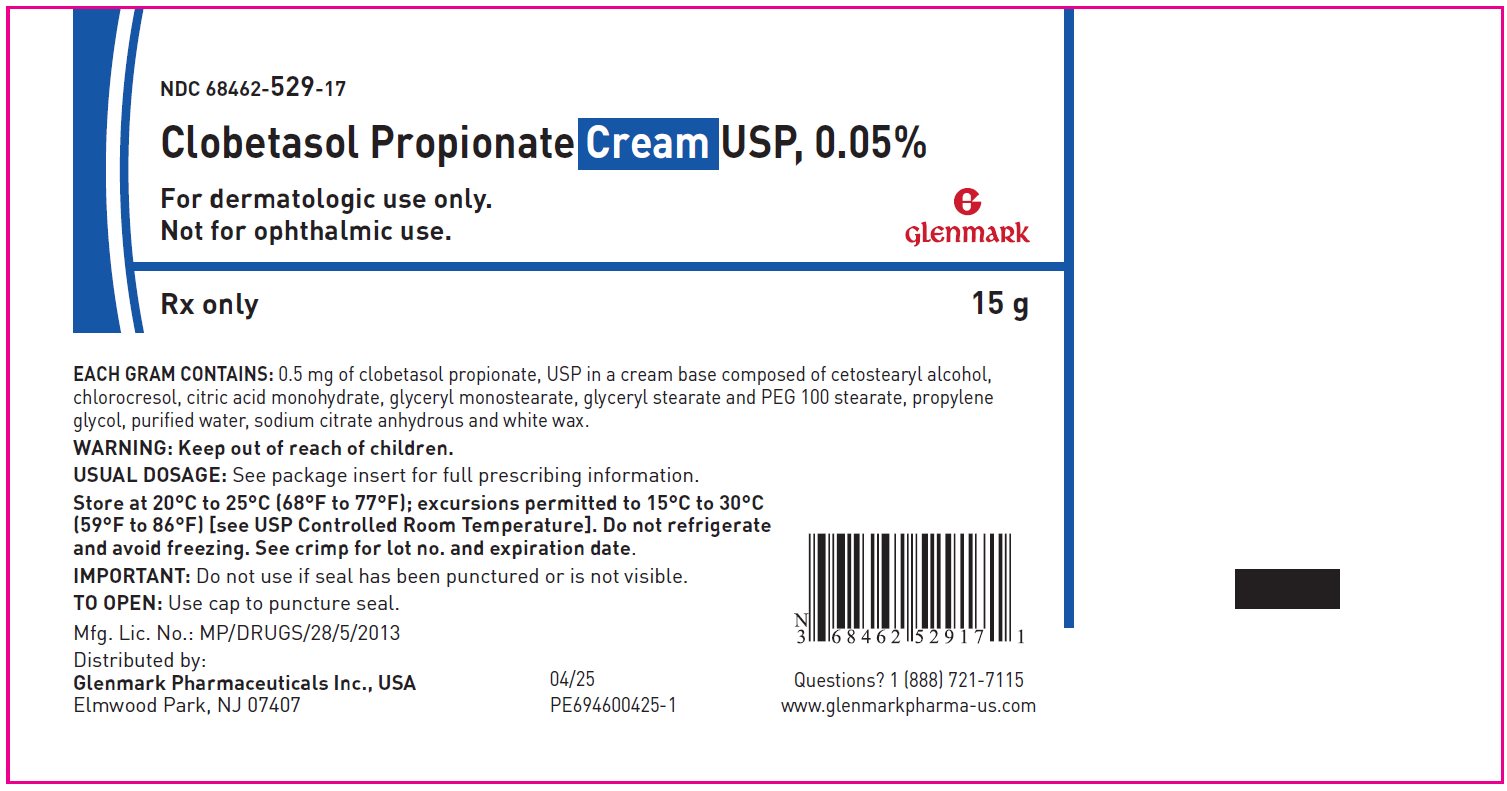 DRUG LABEL: Clobetasol Propionate
NDC: 68462-529 | Form: CREAM
Manufacturer: Glenmark Pharmaceutcials Inc., USA
Category: prescription | Type: HUMAN PRESCRIPTION DRUG LABEL
Date: 20260128

ACTIVE INGREDIENTS: CLOBETASOL PROPIONATE 0.5 mg/1 g
INACTIVE INGREDIENTS: CETOSTEARYL ALCOHOL; CHLOROCRESOL; CITRIC ACID MONOHYDRATE; GLYCERYL MONOSTEARATE; PEG-100 MONOSTEARATE; PROPYLENE GLYCOL; WATER; ANHYDROUS TRISODIUM CITRATE; WHITE WAX

Clobetasol Propionate Cream USP, 0.05%

Rx only

FOR TOPICAL DERMATOLOGIC USE ONLY-

NOT FOR OPHTHALMIC, ORAL, OR INTRAVAGINAL USE.

DESCRIPTION:

Clobetasol Propionate Cream USP, 0.05% contains the active compound clobetasol propionate, USP, a synthetic corticosteroid, for topical dermatologic use. Clobetasol, an analog of prednisolone, has a high degree of glucocorticoid activity and a slight degree of mineralocorticoid activity.

Chemically, clobetasol propionate, USP is 21-chloro-9-fluoro- 11β,17-dihydroxy-16β-methylpregna-1,4-diene-3,20-dione 17-propionate, and it has the following structural formula:

Clobetasol propionate, USP has the molecular formula C25H32CIFO5 and a molecular weight of 466.97 g/mol. It is a white to almost white, crystalline powder, practically insoluble in water, slightly soluble in benzene and diethyl ether; sparingly soluble in ethanol; freely soluble in acetone, in dimethylsulfoxide, in chloroform, in methanol and in dioxane.

Clobetasol Propionate Cream USP, 0.05% contains clobetasol propionate, USP 0.5 mg/g in a cream base composed of cetostearyl alcohol, chlorocresol, citric acid monohydrate, glyceryl monostearate, glyceryl stearate and PEG 100 stearate, propylene glycol, purified water, sodium citrate anhydrous and white wax.

CLINICAL PHARMACOLOGY:

Like other topical corticosteroids, clobetasol propionate has anti-inflammatory, antipruritic, and vasoconstrictive properties. The mechanism of the anti-inflammatory activity of the topical steroids, in general, is unclear. However, corticosteroids are thought to act by the induction of phospholipase A2 inhibitory proteins, collectively called lipocortins. It is postulated that these proteins control the biosynthesis of potent mediators of inflammation such as prostaglandins and leukotrienes by inhibiting the release of their common precursor, arachidonic acid. Arachidonic acid is released from membrane phospholipids by phospholipase A2.

Pharmacokinetics:

The extent of percutaneous absorption of topical corticosteroids is determined by many factors, including the vehicle and the integrity of the epidermal barrier. Occlusive dressing with hydrocortisone for up to 24 hours has not been demonstrated to increase penetration; however, occlusion of hydrocortisone for 96 hours markedly enhances penetration. Topical corticosteroids can be absorbed from normal intact skin. Inflammation and/or other disease processes in the skin may increase percutaneous absorption.

Studies performed with clobetasol propionate cream indicate that they are in the super-high range of potency as compared with other topical corticosteroids.

INDICATIONS AND USAGE:

Clobetasol propionate cream is a super-high potency corticosteroid formulations indicated for the relief of the inflammatory and pruritic manifestations of corticosteroid-responsive dermatoses. Treatment beyond 2 consecutive weeks is not recommended, and the total dosage should not exceed 50 g/week because of the potential for the drug to suppress the hypothalamic-pituitary-adrenal (HPA) axis. Use in pediatric patients under 12 years of age is not recommended.

As with other highly active corticosteroids, therapy should be discontinued when control has been achieved. If no improvement is seen within 2 weeks, reassessment of the diagnosis may be necessary.

CONTRAINDICATIONS:

Clobetasol propionate cream is contraindicated in those patients with a history of hypersensitivity to any of the components of the preparations.

PRECAUTIONS:

General:

Clobetasol propionate cream should not be used in the treatment of rosacea or perioral dermatitis, and should not be used on the face, groin, or axillae.

Systemic absorption of topical corticosteroids can produce reversible HPA axis suppression with the potential for glucocorticosteroid insufficiency after withdrawal from treatment. Manifestations of Cushing’s syndrome, hyperglycemia, and glucosuria can also be produced in some patients by systemic absorption of topical corticosteroids while on therapy.

Patients applying a topical steroid to a large surface area or to areas under occlusion should be evaluated periodically for evidence of HPA axis suppression. This may be done by using the ACTH stimulation, A.M. plasma cortisol, and urinary free cortisol tests. Patients receiving super-potent corticosteroids should not be treated for more than 2 weeks at a time, and only small areas should be treated at any one time due to the increased risk of HPA suppression.

Clobetasol propionate cream produced HPA axis suppression when used at doses as low as 2 g/day for 1 week in patients with eczema.

If HPA axis suppression is noted, an attempt should be made to withdraw the drug, to reduce the frequency of application, or to substitute a less potent corticosteroid. Recovery of HPA axis function is generally prompt upon discontinuation of topical corticosteroids. Infrequently, signs and symptoms of glucocorticosteroid insufficiency may occur that require supplemental systemic corticosteroids. For information on systemic supplementation, see prescribing information for those products.

Pediatric patients may be more susceptible to systemic toxicity from equivalent doses due to their larger skin surface to body mass ratios (see PRECAUTIONS: Pediatric Use).

If irritation develops, clobetasol propionate cream should be discontinued and appropriate therapy instituted. Allergic contact dermatitis with corticosteroids is usually diagnosed by observing a failure to heal rather than noting a clinical exacerbation as with most topical products not containing corticosteroids. Such an observation should be corroborated with appropriate diagnostic patch testing.

If concomitant skin infections are present or develop, an appropriate antifungal or antibacterial agent should be used. If a favorable response does not occur promptly, use of clobetasol propionate cream should be discontinued until the infection has been adequately controlled.

Information for Patients:

Patients using topical corticosteroids should receive the following information and instructions:

1. This medication is to be used as directed by the physician. It is for external use only. Avoid contact with the eyes.
2. This medication should not be used for any disorder other than that for which it was prescribed.
3. The treated skin area should not be bandaged, otherwise covered, or wrapped so as to be occlusive unless directed by the physician.
4. Patients should report any signs of local adverse reactions to the physician.

Laboratory Tests:

The following tests may be helpful in evaluating patients for HPA axis suppression:

ACTH stimulation test
A.M. plasma cortisol test
Urinary free cortisol test

Carcinogenesis, Mutagenesis, Impairment of Fertility:

Long-term animal studies have not been performed to evaluate the carcinogenic potential of clobetasol propionate.

Studies in the rat following subcutaneous administration at dosage levels up to 50 mcg/kg/day revealed that the females exhibited an increase in the number of resorbed embryos and a decrease in the number of living fetuses at the highest dose.

Clobetasol propionate was nonmutagenic in 3 different test systems: the Ames test, the Saccharomyces cerevisiae gene conversion assay, and the E. coli B WP2 fluctuation test.

Pregnancy:

Teratogenic Effects:

Corticosteroids have been shown to be teratogenic in laboratory animals when administered systemically at relatively low dosage levels. Some corticosteroids have been shown to be teratogenic after dermal application to laboratory animals.

Clobetasol propionate has not been tested for teratogenicity when applied topically; however, it is absorbed percutaneously, and when administered subcutaneously it was a significant teratogen in both the rabbit and mouse. Clobetasol propionate has greater teratogenic potential than steroids that are less potent.

Teratogenicity studies in mice using the subcutaneous route resulted in fetotoxicity at the highest dose tested (1 mg/kg) and teratogenicity at all dose levels tested down to 0.03 mg/kg. These doses are approximately 1.4 and 0.04 times, respectively, the human topical dose of clobetasol propionate cream. Abnormalities seen included cleft palate and skeletal abnormalities.

In rabbits, clobetasol propionate was teratogenic at doses of 3 and 10 mcg/kg. These doses are approximately 0.02 and 0.05 times, respectively, the human topical dose of clobetasol propionate cream. Abnormalities seen included cleft palate, cranioschisis, and other skeletal abnormalities.

There are no adequate and well-controlled studies of the teratogenic potential of clobetasol propionate in pregnant women. Clobetasol propionate cream should be used during pregnancy only if the potential benefit justifies the potential risk to the fetus.

Nursing Mothers:

Systemically administered corticosteroids appear in human milk and could suppress growth, interfere with endogenous corticosteroid production, or cause other untoward effects. It is not known whether topical administration of corticosteroids could result in sufficient systemic absorption to produce detectable quantities in human milk. Because many drugs are excreted in human milk, caution should be exercised when clobetasol propionate cream is administered to a nursing woman.

Pediatric Use:

Safety and effectiveness of clobetasol propionate cream in pediatric patients have not been established. Use in pediatric patients under 12 years of age is not recommended. Because of a higher ratio of skin surface area to body mass, pediatric patients are at a greater risk than adults of HPA axis suppression and Cushing’s syndrome when they are treated with topical corticosteroids. They are therefore also at greater risk of adrenal insufficiency during or after withdrawal of treatment. Adverse effects including striae have been reported with inappropriate use of topical corticosteroids in infants and children.

HPA axis suppression, Cushing’s syndrome, linear growth retardation, delayed weight gain, and intracranial hypertension have been reported in children receiving topical corticosteroids. Manifestations of adrenal suppression in children include low plasma cortisol levels and an absence of response to ACTH stimulation. Manifestations of intracranial hypertension include bulging fontanelles, headaches, and bilateral papilledema.

Geriatric Use:

A limited number of patients at or above 65 years of age have been treated with clobetasol propionate cream (n = 231) in US and non-US clinical trials. While the number of patients is too small to permit separate analysis of efficacy and safety, the adverse reactions reported in this population were similar to those reported by younger patients. Based on available data, no adjustment of dosage of clobetasol propionate cream in geriatric patients is warranted.

ADVERSE REACTIONS:

In controlled clinical trials, the most frequent adverse reactions reported for clobetasol propionate cream were burning and stinging sensation in 1% of treated patients. Less frequent adverse reactions were itching, skin atrophy, and cracking and fissuring of the skin.

Cushing’s syndrome has been reported in infants and adults as a result of prolonged use of topical clobetasol propionate formulations.

The following additional local adverse reactions have been reported with topical corticosteroids, and they may occur more frequently with the use of occlusive dressings and higher potency corticosteroids. These reactions are listed in an approximately decreasing order of occurrence: dryness, acneiform eruptions, hypopigmentation, perioral dermatitis, allergic contact dermatitis, secondary infection, irritation, striae, and miliaria.

OVERDOSAGE:

Topically applied clobetasol propionate cream can be absorbed in sufficient amounts to produce systemic effects (see PRECAUTIONS).

DOSAGE AND ADMINISTRATION:

Apply a thin layer of clobetasol propionate cream to the affected skin areas twice daily and rub in gently and completely (see INDICATIONS AND USAGE).

Clobetasol propionate cream are super-high potency topical corticosteroids; therefore, treatment should be limited to 2 consecutive weeks and amounts greater than 50 g/week should not be used.

As with other highly active corticosteroids, therapy should be discontinued when control has been achieved. If no improvement is seen within 2 weeks, reassessment of diagnosis may be necessary.

Clobetasol propionate cream should not be used with occlusive dressings.

Geriatric Use:

In studies where geriatric patients (65 years of age or older, see PRECAUTIONS) have been treated with clobetasol propionate cream, safety did not differ from that in younger patients; therefore, no dosage adjustment is recommended.

HOW SUPPLIED:

Clobetasol Propionate Cream USP, 0.05% is supplied in 15 g tubes (NDC 68462-529-17), 30 g tubes (NDC 68462-529-35), 45 g tubes (NDC 68462-529-47) and 60 g tubes (NDC 68462-529-65).

Store at 20°C to 25°C (68°F to 77°F); excursions permitted to 15°C to 30°C (59°F to 86°F) [see USP Controlled Room Temperature].

Do not refrigerate and avoid freezing.

Rx only

Distributed by:

Glenmark Pharmaceuticals Inc., USA
Elmwood Park, NJ 07407

Questions? 1 (888) 721-7115
www.glenmarkpharma-us.com

April 2025

Package/Label Display Panel

NDC 68462-529-17

Clobetasol Propionate Cream, USP

15 g - Tube

Package/Label Display Panel

NDC 68462-529-17

Clobetasol Propionate Cream, USP

15 g - Carton